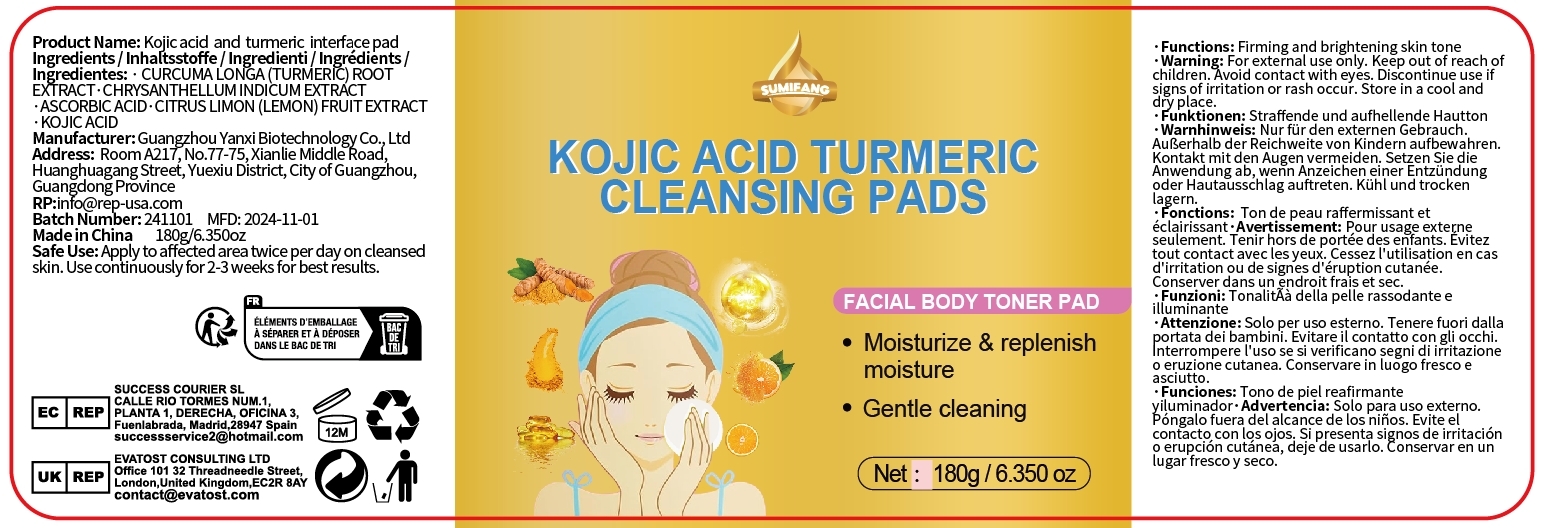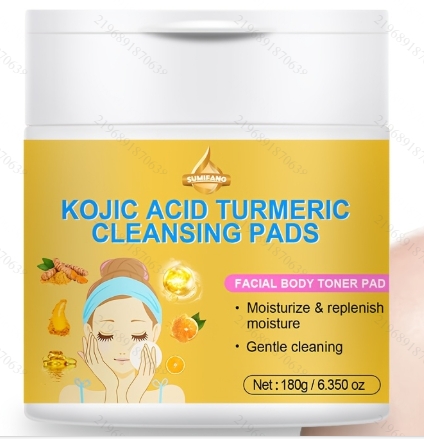 DRUG LABEL: Kojic acid and turmeric interface pad
NDC: 84025-299 | Form: SWAB
Manufacturer: Guangzhou Yanxi Biotechnology Co., Ltd
Category: otc | Type: HUMAN OTC DRUG LABEL
Date: 20241229

ACTIVE INGREDIENTS: KOJIC ACID 3 mg/100 g; ASCORBIC ACID 5 mg/100 g
INACTIVE INGREDIENTS: WATER

DOSAGE AND ADMINISTRATION

Apply to affected area twice per day on cleansedskin.Use continuously for 2-3 weeks for best results.

WARNINGS

keep out of children

INACTIVE INGREDIENT

Aqua

INDICATIONS AND USAGE

for daily face clean

keep out of children

PURPOSE

Firming and brightening skin tone